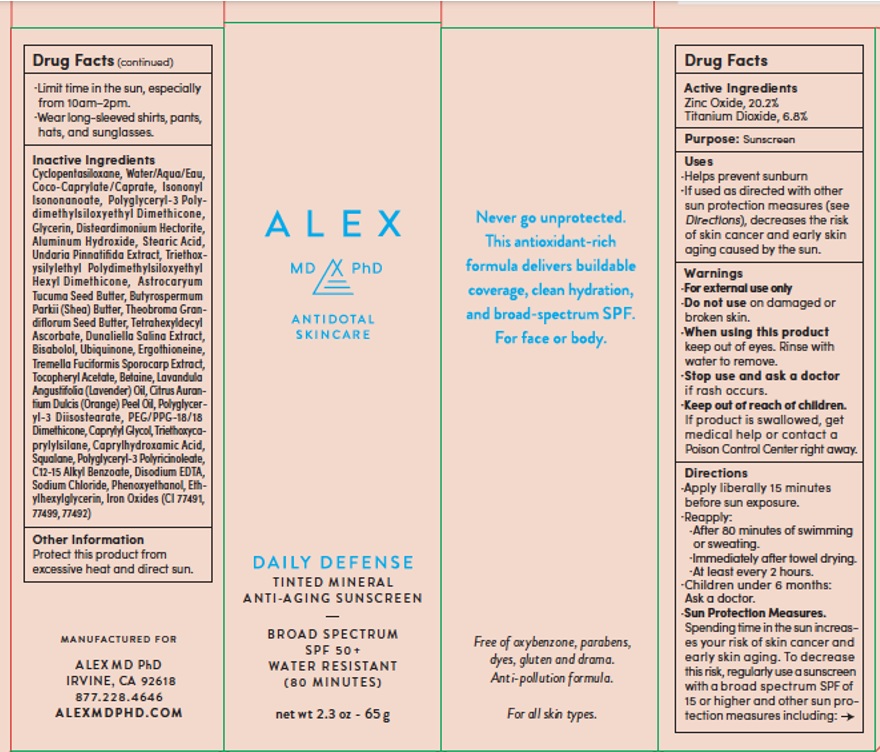 DRUG LABEL: ALEX MD PHD Tinted Mineral Sunscreen
NDC: 78709-002 | Form: CREAM
Manufacturer: PHYSICIAN LABORATORIES INC
Category: otc | Type: HUMAN OTC DRUG LABEL
Date: 20250328

ACTIVE INGREDIENTS: ZINC OXIDE 20.2 g/100 g; TITANIUM DIOXIDE 6.8 g/100 g
INACTIVE INGREDIENTS: POLYGLYCERYL-3 PENTARICINOLEATE; ALKYL (C12-15) BENZOATE; EDETATE DISODIUM; SODIUM CHLORIDE; PHENOXYETHANOL; ETHYLHEXYLGLYCERIN; FERRIC OXIDE RED; FERROSOFERRIC OXIDE; FERRIC OXIDE YELLOW; ERGOTHIONEINE; TREMELLA FUCIFORMIS FRUITING BODY; .ALPHA.-TOCOPHEROL ACETATE; BETAINE; LAVENDER OIL; ORANGE OIL, COLD PRESSED; POLYGLYCERYL-3 DIISOSTEARATE; PEG/PPG-18/18 DIMETHICONE; CAPRYLYL GLYCOL; TRIETHOXYCAPRYLYLSILANE; CAPRYLHYDROXAMIC ACID; SQUALANE; CYCLOMETHICONE 5; WATER; COCOYL CAPRYLOCAPRATE; ISONONYL ISONONANOATE; POLYGLYCERYL-3 POLYDIMETHYLSILOXYETHYL DIMETHICONE (4000 MPA.S); GLYCERIN; DISTEARDIMONIUM HECTORITE; ALUMINUM HYDROXIDE; STEARIC ACID; UNDARIA PINNATIFIDA; TRIETHOXYSILYLETHYL POLYDIMETHYLSILOXYETHYL HEXYL DIMETHICONE; ASTROCARYUM VULGARE KERNEL OIL; SHEA BUTTER; THEOBROMA GRANDIFLORUM SEED BUTTER; TETRAHEXYLDECYL ASCORBATE; DUNALIELLA SALINA; LEVOMENOL; UBIDECARENONE

Active Ingredient

Zinc Oxide, 20.2%
Titanium Dioxide, 6.8%

Purpose

Sunscreen

Uses

- Helps prevent sunburn
- If used as directed with other sun protection measures (see Directions), decreases the risk of skin cancer and early

Warnings

- For external use only
- Do not use ondamaged or broken skin.
- When using this productkeep out of eyes. Rinse with water to remove.
- Stop use and ask a doctorif rash occurs.
- Keep out of reach of children.If product is swallowed, get medical help or contact a Poison Control Center right away.

Directions

- Apply liberally 15 minutes before sun exposure.
- Reapply:
- After 80 minutes of swimmingor sweating.
- Immediately after towel drying.
- At least every 2 hours.
- Children under 6 months: Ask a doctor.
- Sun Protection Measures.

Spending time in the sun increases your risk of skin cancer and early skin aging. To decrease this risk, regularly use a sunscreen
with a broad spectrum SPF of 15 or higher and other sun protection measures including:
•Limit time in the sun, especially from 10am–2pm.
•Wear long-sleeved shirts, pants, hats, and sunglasses.

Inactive igredients

Cyclopentasiloxane, Water/Aqua/Eau, Coco-Caprylate /Caprate, Isononyl Isononanoate, Polyglyceryl-3 Polydimethylsiloxyethyl
Dimethicone, Glycerin, Disteardimonium Hectorite, Aluminum Hydroxide, Stearic Acid, Undaria Pinnatifida Extract, Triethoxysilylethyl
Polydimethylsiloxyethyl Hexyl Dimethicone, Astrocaryum Tucuma Seed Butter, Butyrospermum Parkii (Shea) Butter, Theobroma Grandiflorum
Seed Butter, Tetrahexyldecyl Ascorbate, Dunaliella Salina Extract, Bisabolol, Ubiquinone, Ergothioneine,Tremella Fuciformis Sporocarp Extract,
Tocopheryl Acetate, Betaine, Lavandula Angustifolia (Lavender) Oil, Citrus Aurantium Dulcis (Orange) Peel Oil, Polyglyceryl-3 Diisostearate, PEG/PPG-18/18 Dimethicone, Caprylyl Glycol, Triethoxycaprylylsilane, Caprylhydroxamic Acid, Squalane, Polyglyceryl-3 Polyricinoleate,
C12-15 Alkyl Benzoate, Disodium EDTA, Sodium Chloride, Phenoxyethanol, Ethylhexylglycerin, Iron Oxides (CI 77491, 77499, 77492)

Other information

Protect this product from excessive heat and direct sun.